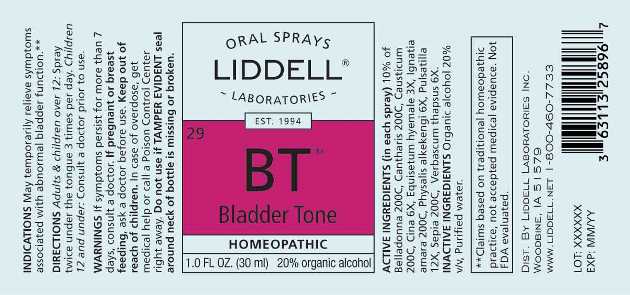 DRUG LABEL: Bladder Tone
NDC: 50845-0271 | Form: SPRAY
Manufacturer: Liddell Laboratories, Inc.
Category: homeopathic | Type: HUMAN OTC DRUG LABEL
Date: 20241104

ACTIVE INGREDIENTS: ATROPA BELLADONNA 200 [hp_C]/1 mL; LYTTA VESICATORIA 200 [hp_C]/1 mL; CAUSTICUM 200 [hp_C]/1 mL; ARTEMISIA CINA PRE-FLOWERING TOP 6 [hp_X]/1 mL; EQUISETUM HYEMALE WHOLE 3 [hp_X]/1 mL; STRYCHNOS IGNATII SEED 200 [hp_C]/1 mL; PHYSALIS ALKEKENGI FRUIT 6 [hp_X]/1 mL; PULSATILLA PRATENSIS WHOLE 12 [hp_X]/1 mL; SEPIA OFFICINALIS JUICE 200 [hp_C]/1 mL; VERBASCUM THAPSUS WHOLE 6 [hp_X]/1 mL
INACTIVE INGREDIENTS: WATER; ALCOHOL

DRUG FACTS:

ACTIVE INGREDIENTS:

(in each spray) 10% of Belladonna 200C, Cantharis 200C, Causticum 200C, Cina 6X, Equisetum Hyemale 3X, Ignatia Amara 200C, Physalis Alkekengi 6X, Pulsatilla (Pratensis) 12X, Sepia 200C, Verbascum Thapsus 6X.

INDICATIONS:

May temporarily relieve symptoms associated with abnormal bladder function.**

**Claims based on traditional homeopathic practice, not accepted medical evidence. Not FDA evaluated.

WARNINGS:

If symptoms persist for more than 7 days, consult a doctor.

If pregnant or breast feeding, ask a doctor before use.

Keep out of reach of children. In case of overdose, get medical help or call a Poison Control Center right away.

Do not use if TAMPER EVIDENT seal around neck of bottle is missing or broken.

Keep out of reach of children. In case of overdose, get medical help or call a Poison Control Center right away.

DIRECTIONS:

Adults and children over 12: Spray twice under the tongue 3 times per day.

Children 12 and under: Consult a doctor prior to use.

INDICATIONS:

May temporarily relieve symptoms associated with abnormal bladder function.**

**Claims based on traditional homeopathic practice, not accepted medical evidence. Not FDA evaluated.

INACTIVE INGREDIENTS:

Organic alcohol 20% v/v, Purified water.

QUESTIONS:

DIST. BY LIDDELL LABORATORIES INC.

WOODBINE, IA 51579

WWW.LIDDELL.NET 1-800-460-7733

PACKAGE LABEL DISPLAY:

ORAL SPRAYS

LIDDELL LABORATORIES

EST. 1994

BLADDER TONE

HOMEOPATHIC

1.0 FL. OZ. (30 ml)